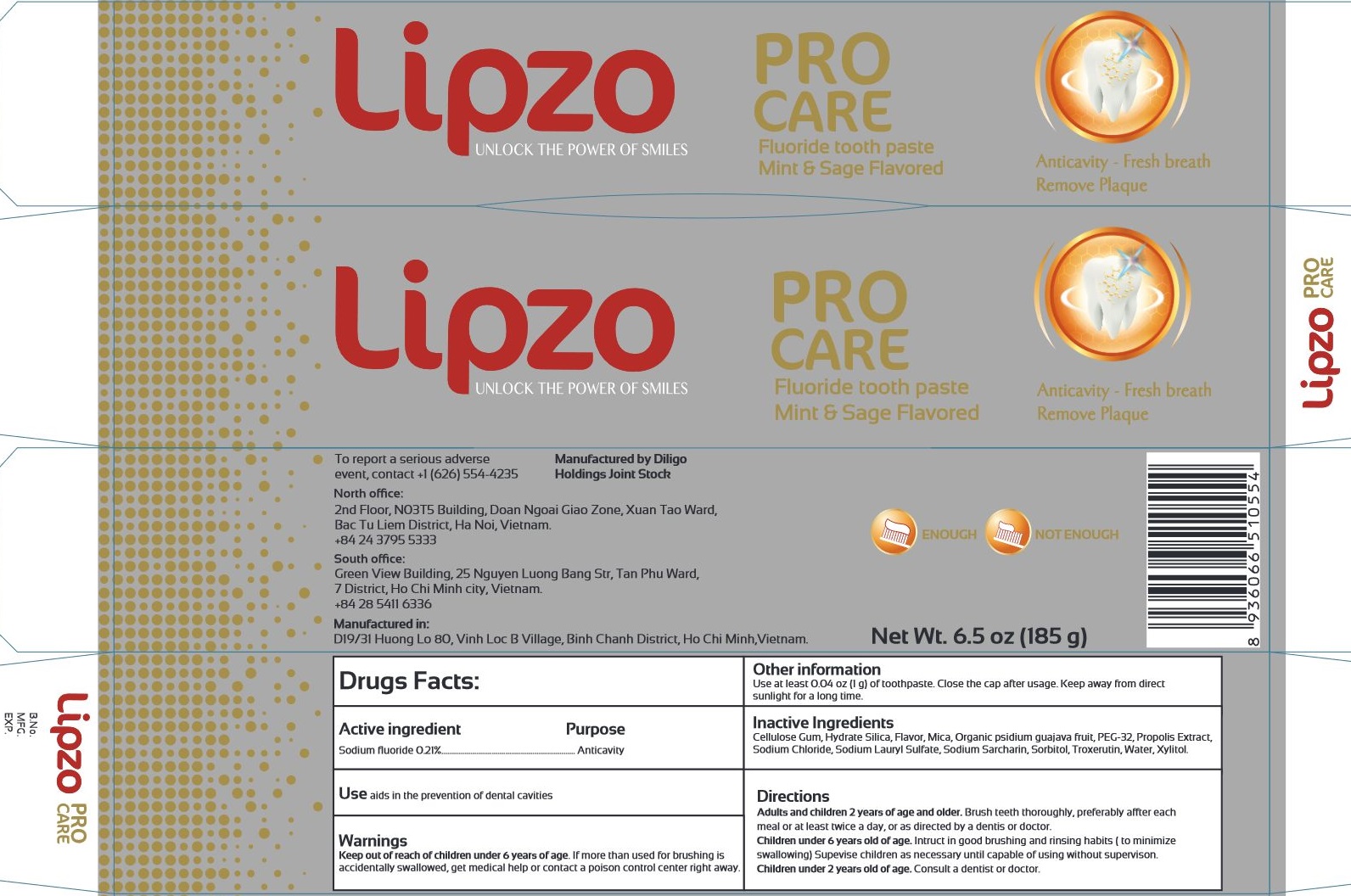 DRUG LABEL: Pro Care Flouride
NDC: 78989-001 | Form: GEL
Manufacturer: DILIGO HOLDINGS JOINT STOCK COMPANY
Category: otc | Type: HUMAN OTC DRUG LABEL
Date: 20200810

ACTIVE INGREDIENTS: SODIUM FLUORIDE 2.1 mg/1 g
INACTIVE INGREDIENTS: CARBOXYMETHYLCELLULOSE SODIUM, UNSPECIFIED; HYDRATED SILICA; METHYL SALICYLATE; MICA; POLYETHYLENE GLYCOL 1600; PROPOLIS WAX; SODIUM CHLORIDE; SODIUM LAURYL SULFATE; SACCHARIN SODIUM; SORBITOL; TROXERUTIN; WATER; XYLITOL

Pro Care Flouride Toothpaste

Active ingredient

Sodium fluoride 0.21%

Purpose

Anticavity

Use

aids in the prevention of dental cavities

Warnings

Keep out of reach of children under 6 years of age.

If more than used for brushing is accidentally swallowed, get medical help or contact a poison control center right away.

Other information

Use at least 0.04 oz (1 g) of toothpaste. Close the cap after usage. Keep away from direct sunlight for a long time.

Inactive Ingredients

Cellulose Gum, Hydrate Silica, Flavor, Mica, Organic psidium guajava fruit, PEG-32, Propolis Extract, Sodium Chloride, Sodium Lauryl Sulfate, Sodium Sarcharin, Sorbitol, Troxerutin, Water, Xylitol.

Directions

Adults and children 2 years of age and older. Brush teeth thoroughly, preferably after each meal or at least twice a day, or as directed by a dentis or doctor.
Children under 6 years old of age. Intruct in good brushing and rinsing habits (to minimize swallowing) Supevise children as necessary until capable of using without supervison.
Children under 2 years old of age. Consult a dentist or doctor.